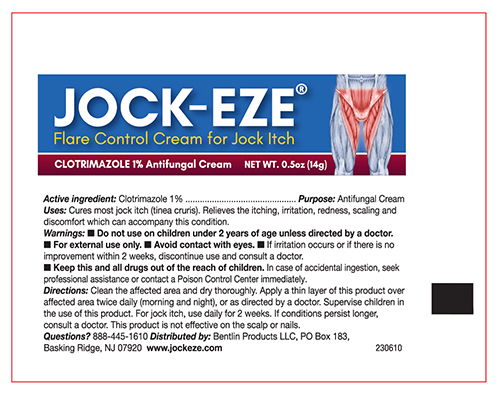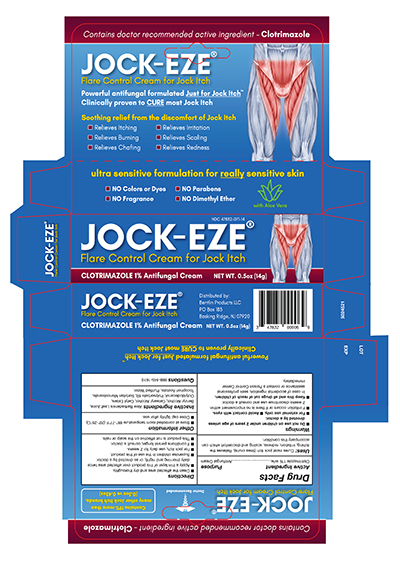 DRUG LABEL: JOCK-EZE
NDC: 47832-071 | Form: CREAM
Manufacturer: Bentlin Products LLC
Category: otc | Type: HUMAN OTC DRUG LABEL
Date: 20231030

ACTIVE INGREDIENTS: CLOTRIMAZOLE 10 mg/1 g
INACTIVE INGREDIENTS: WATER; CETOSTEARYL ALCOHOL; POLYSORBATE 60; BENZYL ALCOHOL; SORBITAN MONOSTEARATE; .ALPHA.-TOCOPHEROL ACETATE; ALOE VERA LEAF; OCTYLDODECANOL; CETYL PALMITATE

JOCK-EZE Clotrimazole Cream

Drug Facts

Active ingredient

Clotrimazole 1 %

Purpose

Antifungal Cream

Uses

Cures most jock itch (tinea cruris). Relieves the itching, irritation, redness, scaling and discomfort which can accompany these conditions.

Warnings

KEEP OUT OF REACH OF CHILDREN

- Keep this and all drugs out of reach of children. In case of accidental ingestion, seek professional assistance or contact a Poison Control Center immediately.

Directions

- Clean the affected area and dry thoroughly.
- Apply a thin layer of this product over affected area twice daily (morning and night), or as directed by a doctor.
- Supervise children in the use of this product.
- For jock itch, use daily for 2 weeks.
- If conditions persist longer, consult a doctor.
- This product is not effective on the scalp or nails.

Other information

- Store at controlled room temperature 68°-77°F (20°-25°C).
- Close cap tightly after use.

Inactive ingredients

Aloe Barbadensis Leaf Juice, Benzyl Alcohol, Cetearyl Alcohol, Cetyl Esters, Octyldodecanol, Polysorbate 60, Sorbitan Monostearate, Tocopheryl Acetate, Purified Water.

Questions?

888-445-1610

Principal Display Panel – 0.5oz Tube

JOCK-EZE NDC 47832-071-14

Flare Control Cream for Jock Itch

Clotrimazole 1% Antifungal Cream

NET WT. 0.5oz (14g)

Principal Display Panel – 0.5oz Carton

NDC 47382-071-14

JOCK-EZE

Flare Control Cream for Jock Itch

Clotrimazole 1% Antifungal Cream

NET WT. 0.5oz (14g)